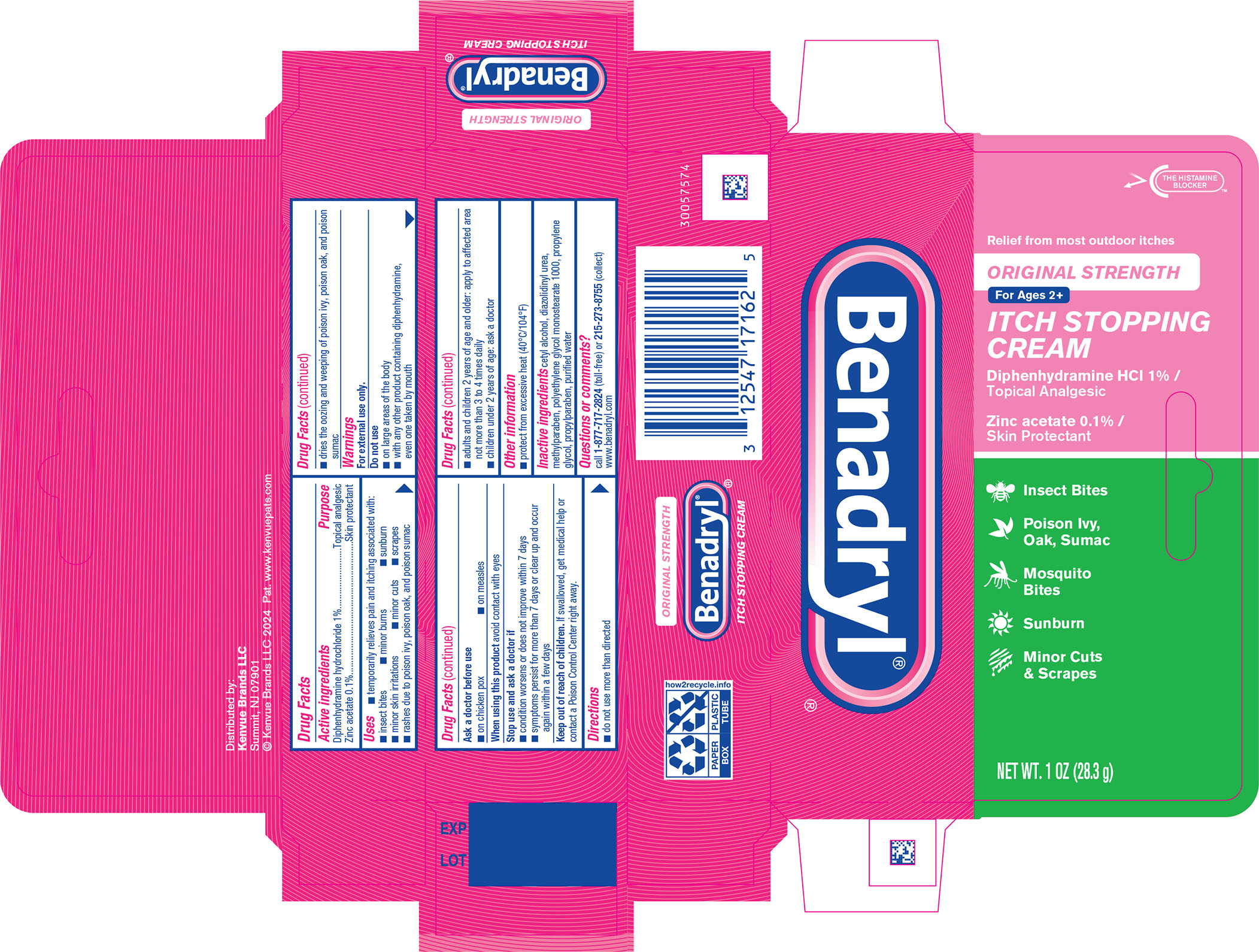 DRUG LABEL: Benadryl Original Strength Itch Stopping
NDC: 69968-0625 | Form: CREAM
Manufacturer: Kenvue Brands LLC
Category: otc | Type: HUMAN OTC DRUG LABEL
Date: 20241126

ACTIVE INGREDIENTS: DIPHENHYDRAMINE HYDROCHLORIDE 10 mg/1 g; ZINC ACETATE 1 mg/1 g
INACTIVE INGREDIENTS: CETYL ALCOHOL; DIAZOLIDINYL UREA; METHYLPARABEN; PROPYLENE GLYCOL; PROPYLPARABEN; WATER

Benadryl® ORIGINAL STRENGTH ITCH STOPPING CREAM

Drug Facts

ACTIVE INGREDIENT

Active ingredients | Purpose
Diphenhydramine hydrochloride 1% | Topical analgesic
Zinc acetate 0.1% | Skin protectant

Uses

- temporarily relieves pain and itching associated with:
- insect bites
- minor burns
- sunburn
- minor skin irritations
- minor cuts
- scrapes
- rashes due to poison ivy, poison oak, and poison sumac
- dries the oozing and weeping of poison ivy, poison oak and poison sumac

Warnings

For external use only.

Do not use

- on large areas of the body
- with any other product containing diphenhydramine, even one taken by mouth

Ask a doctor before use

- on chicken pox
- on measles

When using this product avoid contact with eyes

Stop use and ask a doctor if

- condition worsens or does not improve within 7 days
- symptoms persist for more than 7 days or clear up and occur again within a few days

Keep out of reach of children. If swallowed, get medical help or contact a Poison Control Center right away.

Directions

- do not use more than directed
- adults and children 2 years of age and older: apply to affected area not more than 3 to 4 times daily
- children under 2 years of age: ask a doctor

Other information

- protect from excessive heat (40°C/104°F)

Inactive ingredients

cetyl alcohol, diazolidinyl urea, methylparaben, polyethylene glycol monostearate 1000, propylene glycol, propylparaben, purified water

Questions?

call 1-877-717-2824 (toll-free) or 215-273-8755 (collect) www.benadryl.com

Distributed by:
Kenvue Brands LLC
Summit, NJ 07901

PRINCIPAL DISPLAY PANEL - 28.3 g Tube Carton

Benadryl®®

THE HISTAMINE BLOCKERTM

Relief from most outdoor itches

ORIGINAL STRENGTH

For Ages 2+

ITCH STOPPING

CREAM

Diphenhydramine HCl 1%/

Topical Analgesic

Zinc acetate 0.1% /

Skin Protectant

Insect Bites

Poison Ivy,

Oak, Sumac

Mosquito

Bites

Sunburn

Minor Cuts

& Scrapes

NET WT. 1 OZ (28.3g)